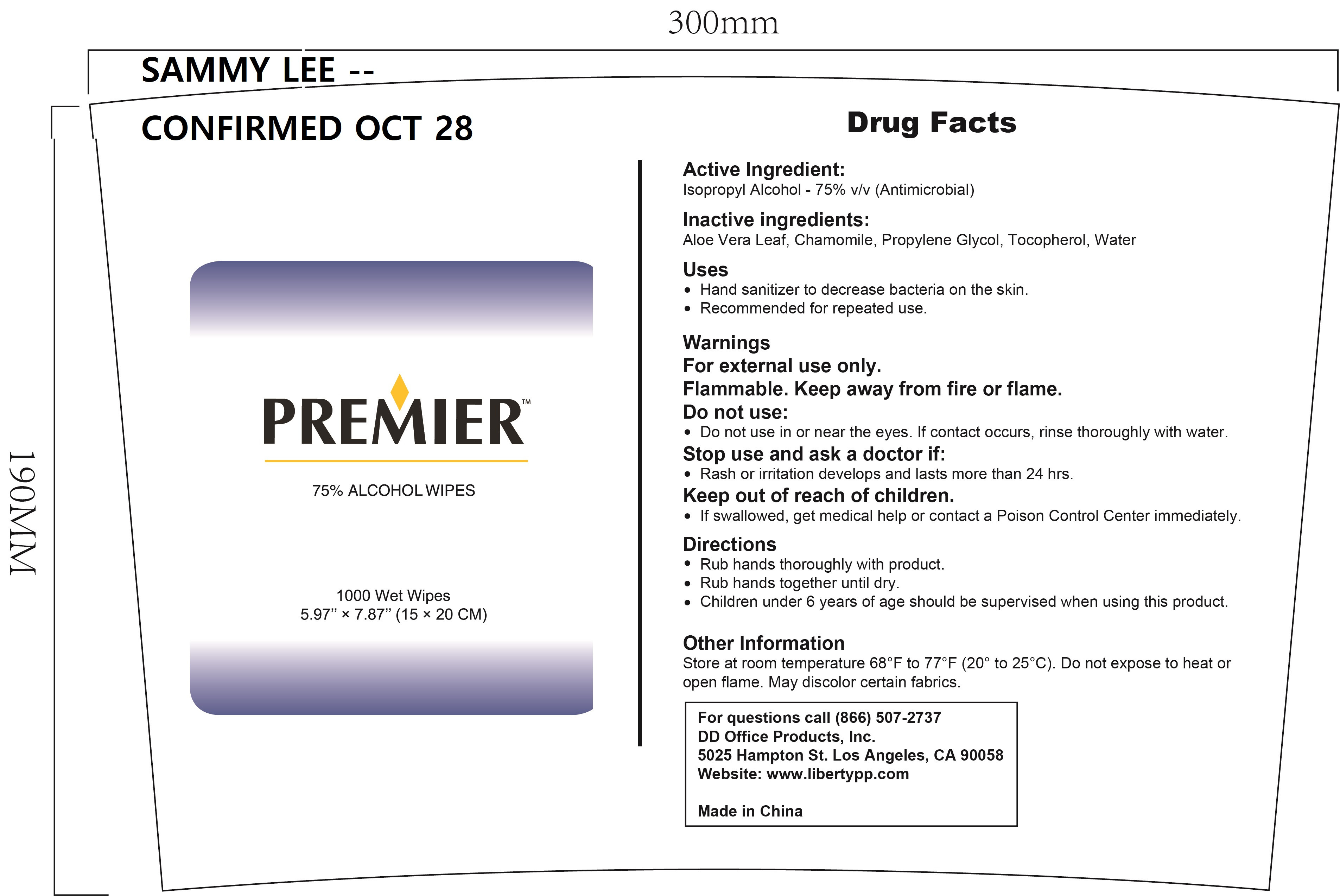 DRUG LABEL: 1000 WET WIPES
NDC: 55415-006 | Form: CLOTH
Manufacturer: JIANGSU MEIFAN BIOTECHNOLOGY CO., LTD.
Category: otc | Type: HUMAN OTC DRUG LABEL
Date: 20240320

ACTIVE INGREDIENTS: ISOPROPYL ALCOHOL 2825 g/1000 1
INACTIVE INGREDIENTS: ALOE VERA LEAF; WATER; TOCOPHEROL; PROPYLENE GLYCOL; CHAMOMILE

55415-06

INDICATIONS AND USAGE

Hand sanitizer to decrease bacteria on the skin

Recommended for repeated use.

DOSAGE AND ADMINISTRATION

Rub hands thoroughly with product.

Rub hands together until dry.

Children under 6 years of age should be supervised when using this product.

INACTIVE INGREDIENT

Aloe Vera Leaf

Chamomile

Propylene Glycol

Tocopherol

Water

ACTIVE INGREDIENT

ISOPROPYL ALCOHOL

KEEP OUT OF REACH OF CHILDREN

lf swallowed, get medical help or contact a Poison Control Center immediately.

PURPOSE

Disinfection
Sterilization
No Rinseing

STORAGE AND HANDLING

Store at room temperature 68°F to 77°F(20° to 25°C).

STOP USE

Rash or irritation develops and lasts more than 24 hrs.

WARNINGS

For external use only.Flammable.Keep away from fire or flame.